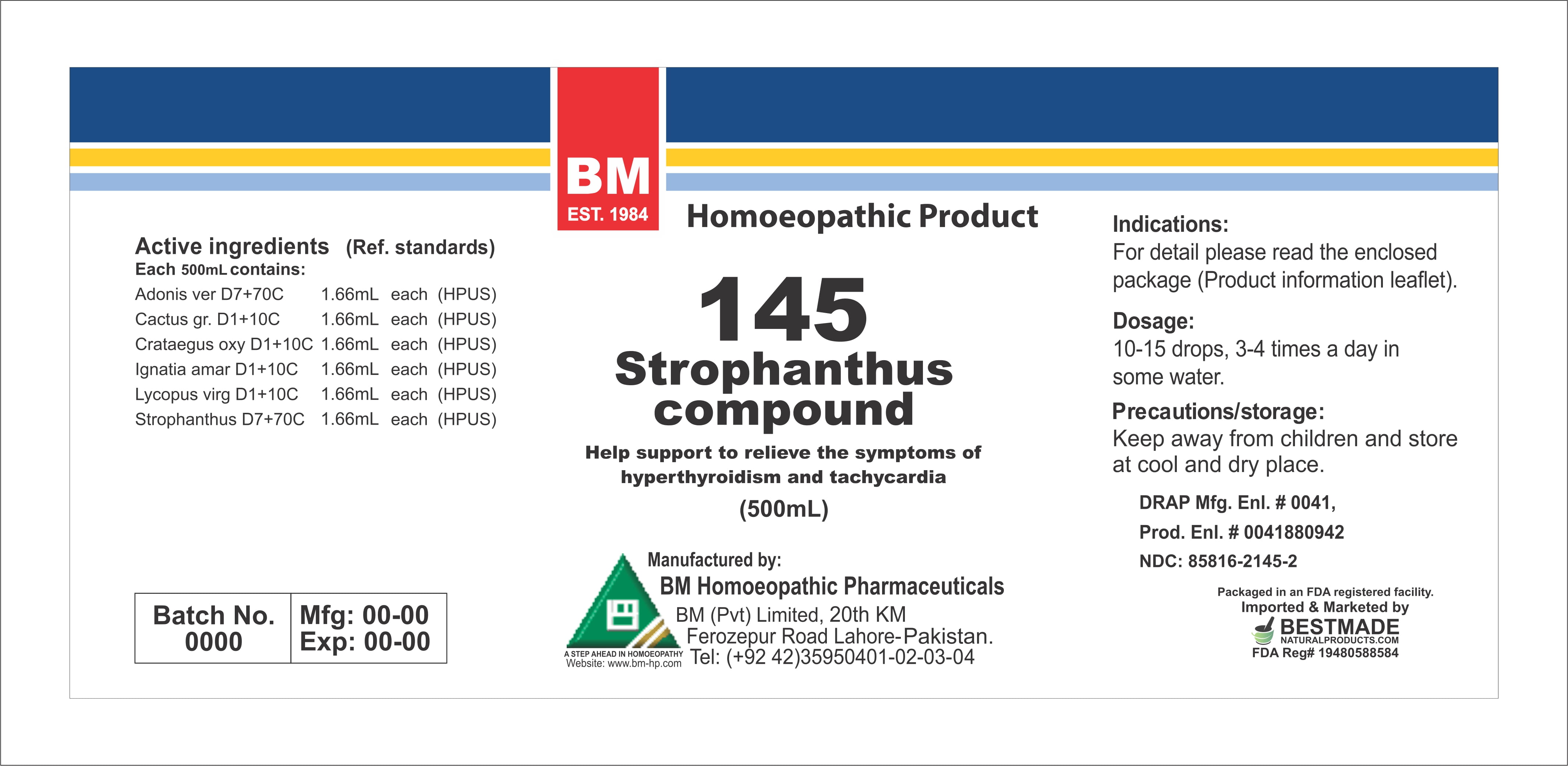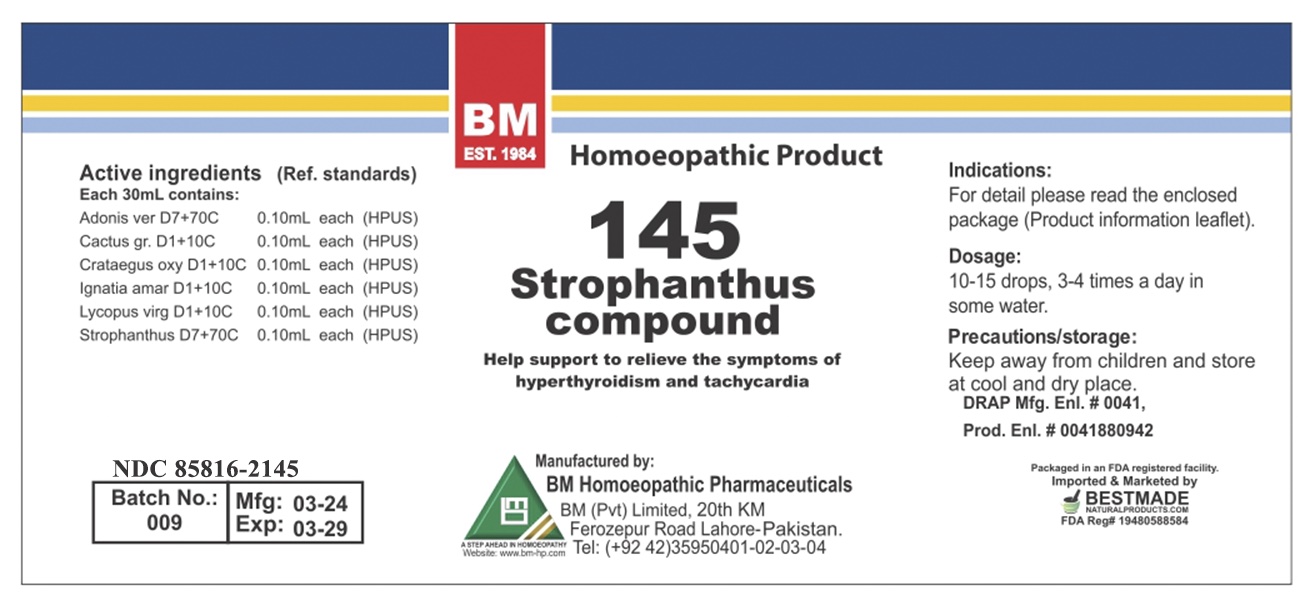 DRUG LABEL: STROPHANTHUS
NDC: 85816-2145 | Form: LIQUID
Manufacturer: BM Private Limited
Category: homeopathic | Type: HUMAN OTC DRUG LABEL
Date: 20260212

ACTIVE INGREDIENTS: ADONIS VERNALIS FLOWERING TOP 7 [hp_X]/1 mL; CRATAEGUS LAEVIGATA WHOLE 1 [hp_X]/1 mL; LYCOPUS VIRGINICUS 1 [hp_X]/1 mL; SELENICEREUS GRANDIFLORUS STEM 1 [hp_X]/1 mL; STROPHANTHUS HISPIDUS SEED 7 [hp_X]/1 mL; STRYCHNOS IGNATII SEED 1 [hp_X]/1 mL
INACTIVE INGREDIENTS: ALCOHOL 0.96 mL/1 mL

BM HOMEOPATHIC REMEDY LIQUIDS STROPHANTHUS/ BM145

DOSAGE AND ADMINISTRATION

10-15 drops, 3-4 times a day in some water

ACTIVE INGREDIENT

Adonis vern, cactus grand, crataegus oxy, ignatia amara, lycopus virg, strophantus

INACTIVE INGREDIENT

ALCOHOL

INDICATIONS AND USAGE

For detail, please read the enclosed package (product information leaflet)

PURPOSE

For detail, please read the enclosed package (product information leaflet)

KEEP OUT OF REACH OF CHILDREN

Precautions/storage:
Keep away from children and store at cool and dry place.

WARNINGS

Precautions/storage:
Keep away from children and store at cool and dry place.

Package 1:

Package 2: